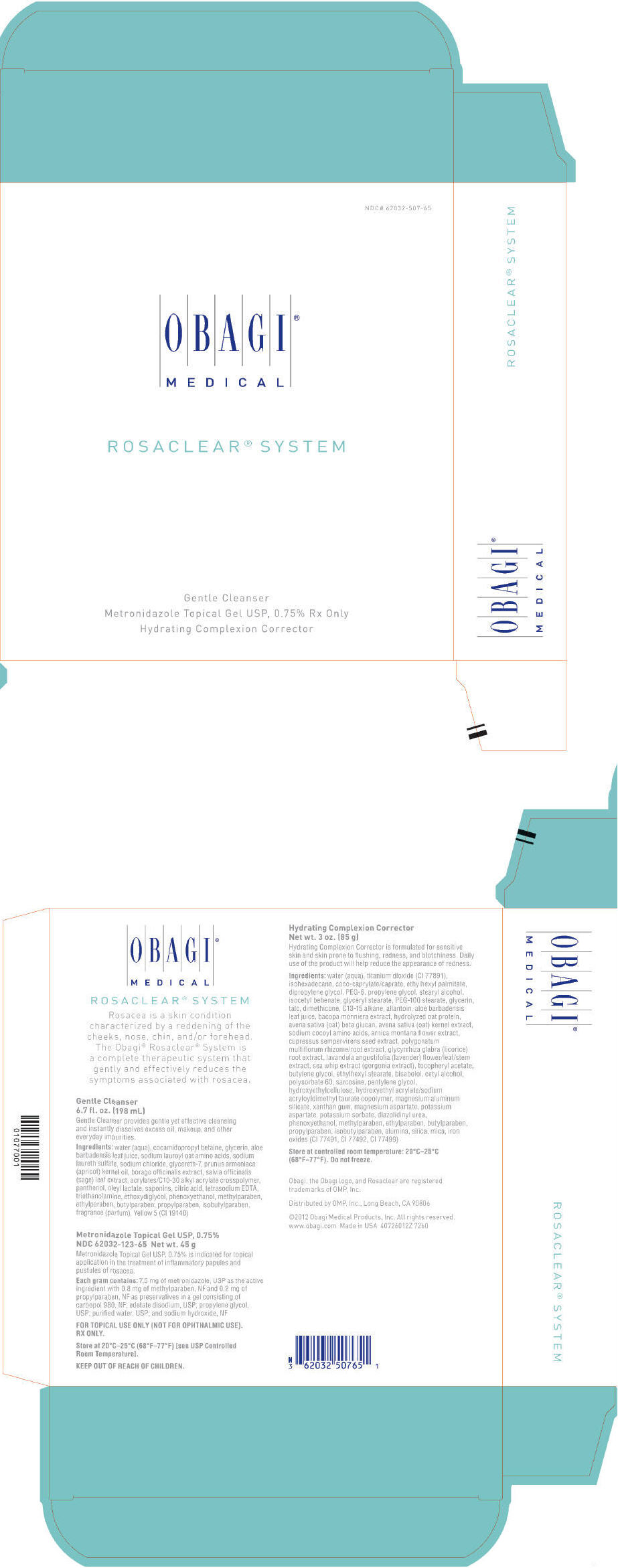 DRUG LABEL: ROSACLEAR SYSTEM
NDC: 62032-507 | Form: KIT | Route: TOPICAL
Manufacturer: OMP, INC.
Category: prescription | Type: HUMAN PRESCRIPTION DRUG LABEL
Date: 20130307

ACTIVE INGREDIENTS: METRONIDAZOLE 7.5 mg/1 g
INACTIVE INGREDIENTS: EDETATE DISODIUM; METHYLPARABEN; PROPYLPARABEN; PROPYLENE GLYCOL; WATER; SODIUM HYDROXIDE; CARBOMER HOMOPOLYMER TYPE C (ALLYL PENTAERYTHRITOL CROSSLINKED)

ROSACLEAR® SYSTEM

Gentle Cleanser 6.7 fl. oz. (198 mL)

Gentle Cleanser provides gentle yet effective cleansing and instantly dissolves excess oil, makeup, and other everyday impurities.

Ingredients

water (aqua), cocamidopropyl betaine, glycerin, aloe barbadensis leaf juice, sodium lauroyl oat amino acids, sodium laureth sulfate, sodium chloride, glycereth-7, prunus armeniaca (apricot) kernel oil, borago officinalis extract, salvia officinalis (sage) leaf extract, acrylates/C10-30 alkyl acrylate crosspolymer, panthenol, oleyl lactate, saponins, citric acid, tetrasodium EDTA, triethanolamine, ethoxydiglycol, phenoxyethanol, methylparaben, ethylparaben, butylparaben, propylparaben, isobutylparaben, fragrance (parfum), Yellow 5 (CI 19140)

Metronidazole Topical Gel USP, 0.75% NDC 62032-123-65 Net wt. 45 g

Metronidazole Topical Gel USP, 0.75% is indicated for topical application in the treatment of inflammatory papules and pustules of rosacea.

Each gram contains

7.5 mg of metronidazole, USP as the active ingredient with 0.8 mg of methylparaben, NF and 0.2 mg of propylparaben, NF as preservatives in a gel consisting of carbopol 980, NF; edetate disodium, USP; propylene glycol, USP; purified water, USP; and sodium hydroxide, NF

FOR TOPICAL USE ONLY (NOT FOR OPHTHALMIC USE).
RX ONLY.

HOW SUPPLIED

STORAGE AND HANDLING

Store at 20°C–25°C (68°F–77°F) [see USP Controlled Room Temperature].

KEEP OUT OF REACH OF CHILDREN.

Hydrating Complexion Corrector Net wt. 3 oz. (85 g)

Hydrating Complexion Corrector is formulated for sensitive skin and skin prone to flushing, redness, and blotchiness. Daily use of the product will help reduce the appearance of redness.

Ingredients

water (aqua), titanium dioxide (CI 77891), isohexadecane, coco-caprylate/caprate, ethylhexyl palmitate, dipropylene glycol, PEG-6, propylene glycol, stearyl alcohol, isocetyl behenate, glyceryl stearate, PEG-100 stearate, glycerin, talc, dimethicone, C13-15 alkane, allantoin, aloe barbadensis leaf juice, bacopa monniera extract, hydrolyzed oat protein, avena sativa (oat) beta glucan, avena sativa (oat) kernel extract, sodium cocoyl amino acids, arnica montana flower extract, cupressus sempervirens seed extract, polygonatum multiflorum rhizome/root extract, glycyrrhiza glabra (licorice) root extract, lavandula angustifolia (lavender) flower/leaf/stem extract, sea whip extract (gorgonia extract), tocopheryl acetate, butylene glycol, ethylhexyl stearate, bisabolol, cetyl alcohol, polysorbate 60, sarcosine, pentylene glycol, hydroxyethylcellulose, hydroxyethyl acrylate/sodium acryloyldimethyl taurate copolymer, magnesium aluminum silicate, xanthan gum, magnesium aspartate, potassium aspartate, potassium sorbate, diazolidinyl urea, phenoxyethanol, methylparaben, ethylparaben, butylparaben, propylparaben, isobutylparaben, alumina, silica, mica, iron oxides (CI 77491, CI 77492, CI 77499)

HOW SUPPLIED

STORAGE AND HANDLING

Store at controlled room temperature: 20°C–25°C (68°F–77°F). Do not freeze.

Obagi, the Obagi logo, and Rosaclear are registered trademarks of OMP, Inc.

Distributed by OMP, Inc., Long Beach, CA 90806

©2012 Obagi Medical Products, Inc. All rights reserved.
www.obagi.com Made in USA 40726012Z 7260

PRINCIPAL DISPLAY PANEL - Kit Carton

NDC# 62032-507-65

OBAGI®

MEDICAL

ROSACLEAR® SYSTEM

Gentle Cleanser
Metronidazole Topical Gel USP, 0.75% Rx Only
Hydrating Complexion Corrector